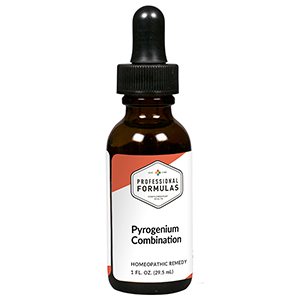 DRUG LABEL: Pyrogenium Combination
NDC: 63083-9239 | Form: LIQUID
Manufacturer: Professional Complementary Health Formulas
Category: homeopathic | Type: HUMAN OTC DRUG LABEL
Date: 20190815

ACTIVE INGREDIENTS: ASCORBIC ACID 3 [hp_X]/29.5 mL; CONIUM MACULATUM FLOWERING TOP 4 [hp_X]/29.5 mL; SOLANUM DULCAMARA WHOLE 4 [hp_X]/29.5 mL; ECHINACEA ANGUSTIFOLIA WHOLE 4 [hp_X]/29.5 mL; HORSE CHESTNUT 6 [hp_X]/29.5 mL; ANTIMONY POTASSIUM TARTRATE 6 [hp_X]/29.5 mL; PROTORTONIA CACTI 6 [hp_X]/29.5 mL; GALIUM APARINE WHOLE 6 [hp_X]/29.5 mL; GENTIANA LUTEA ROOT 6 [hp_X]/29.5 mL; GERANIUM ROBERTIANUM WHOLE 6 [hp_X]/29.5 mL; LACTIC ACID, DL- 6 [hp_X]/29.5 mL; PULSATILLA MONTANA WHOLE 6 [hp_X]/29.5 mL; SULFUR 8 [hp_X]/29.5 mL; ANHYDROUS DIBASIC CALCIUM PHOSPHATE 10 [hp_X]/29.5 mL; FERROSOFERRIC PHOSPHATE 10 [hp_X]/29.5 mL; BOS TAURUS HYPOTHALAMUS 10 [hp_X]/29.5 mL; BEEF LIVER 10 [hp_X]/29.5 mL; BOS TAURUS LYMPH VESSEL 10 [hp_X]/29.5 mL; SUS SCROFA BONE MARROW 10 [hp_X]/29.5 mL; BOS TAURUS SPLEEN 10 [hp_X]/29.5 mL; CORTISONE ACETATE 13 [hp_X]/29.5 mL; BEEF KIDNEY 13 [hp_X]/29.5 mL; MERCURIUS SOLUBILIS 13 [hp_X]/29.5 mL; THYROID, UNSPECIFIED 13 [hp_X]/29.5 mL; BARIUM CARBONATE 28 [hp_X]/29.5 mL; SCABIES LESION LYSATE (HUMAN) 28 [hp_X]/29.5 mL; BOS TAURUS TONSIL 28 [hp_X]/29.5 mL; RANCID BEEF 198 [hp_X]/29.5 mL
INACTIVE INGREDIENTS: ALCOHOL; WATER

R239

ACTIVE INGREDIENTS

Ascorbicum acidum 3X
Conium maculatum 4X
Dulcamara 4X
Echinacea angustifolia 4X
Aesculus hippocastanum 6X
Antimonium tartaricum 6X
Coccus cacti 6X
Galium aparine 6X
Gentiana lutea 6X
Geranium robertianum 6X
L(+) Lacticum acidum 6X
Pulsatilla 6X
Sulphur 8X
Calcarea phosphorica 10X
Ferrum phosphoricum 10X
Hypothalamus 10X
Liver 10X
Lymph 10X
Medulla ossis 10X
Spleen 10X
Cortisone aceticum 13X
Kidney 13X
Mercurius solubilis 13X
Thyroid 13X
Baryta carbonica 28X
Psorinum 28X
Tonsils 28X
Pyrogenium 198X

QUESTIONS

Professional Formulas

PO Box 2034 Lake Oswego, OR 97035

INDICATIONS

For the temporary relief of flu-like symptoms such as low grade fever, chills, muscle aches, congestion, occasional headache, or fatigue.*

PURPOSE

*Claims based on traditional homeopathic practice, not accepted medical evidence. Not FDA evaluated.

WARNINGS

Persistent symptoms may be a sign of a serious condition. If symptoms persist or are accompanied by a fever, rash, or persistent headache, consult a doctor. Keep out of the reach of children. In case of overdose, get medical help or contact a poison control center right away. If pregnant or breastfeeding, ask a healthcare professional before use.

Keep out of the reach of children.

PREGNANCY OR BREAST FEEDING

If pregnant or breastfeeding, ask a healthcare professional before use.

DIRECTIONS

Place drops under tongue 30 minutes before/after meals. Adults and children 12 years and over: Take 10 drops up to 3 times per day. Consult a physician for use in children under 12 years of age.

OTHER INFORMATION

Tamper resistant. If seal is broken, do not use. After opening, close container tightly and store at room temperature away from heat.

INACTIVE INGREDIENTS

40% ethanol, purified water.

LABEL

Est 1985

Professional Formulas

Complementary Health

Pyrogenium Combination

Homeopathic Remedy

1 FL. OZ. (29.5 mL)